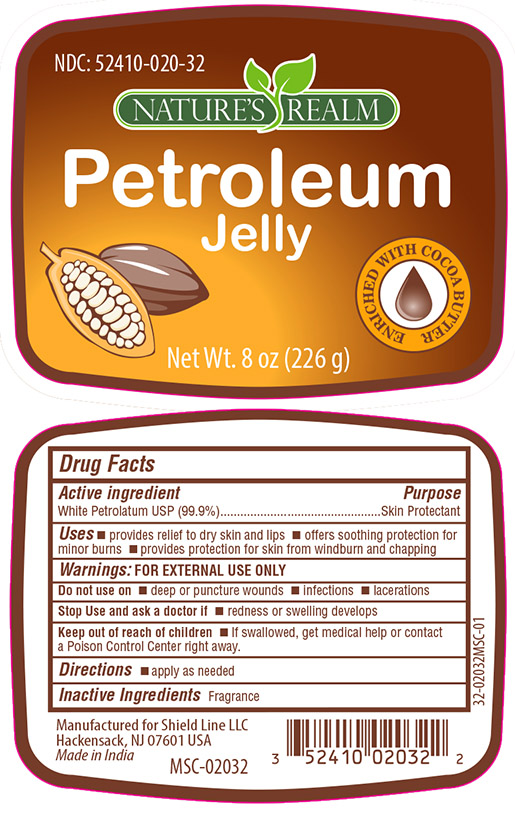 DRUG LABEL: Petrolatum Jelly with Cocoa Butter
NDC: 52410-0203 | Form: JELLY
Manufacturer: Shield Line LLC
Category: otc | Type: HUMAN OTC DRUG LABEL
Date: 20210224

ACTIVE INGREDIENTS: PETROLATUM 99.9 g/100 g
INACTIVE INGREDIENTS: WATER

DRUG FACTS

White Petrolatum USP 99.9%

PURPOSE

Skin Protectant

Uses

- provides relief to dry skin and lips
- offers soothing protection for minor burns
- provides protection for skin from wind burn and chapping

Warnings

FOR EXTERNAL USE ONLY

Do not use on

- deep or puncture wounds
- infections
- lacerations

Stop Use and ask a doctor if

- redness or swelling develops

Keep out of reach of children

- If swallowed, get medical help or contact a Poison Control Center right away.

Directions

- apply as needed

Inactive Ingredients

Fragrance